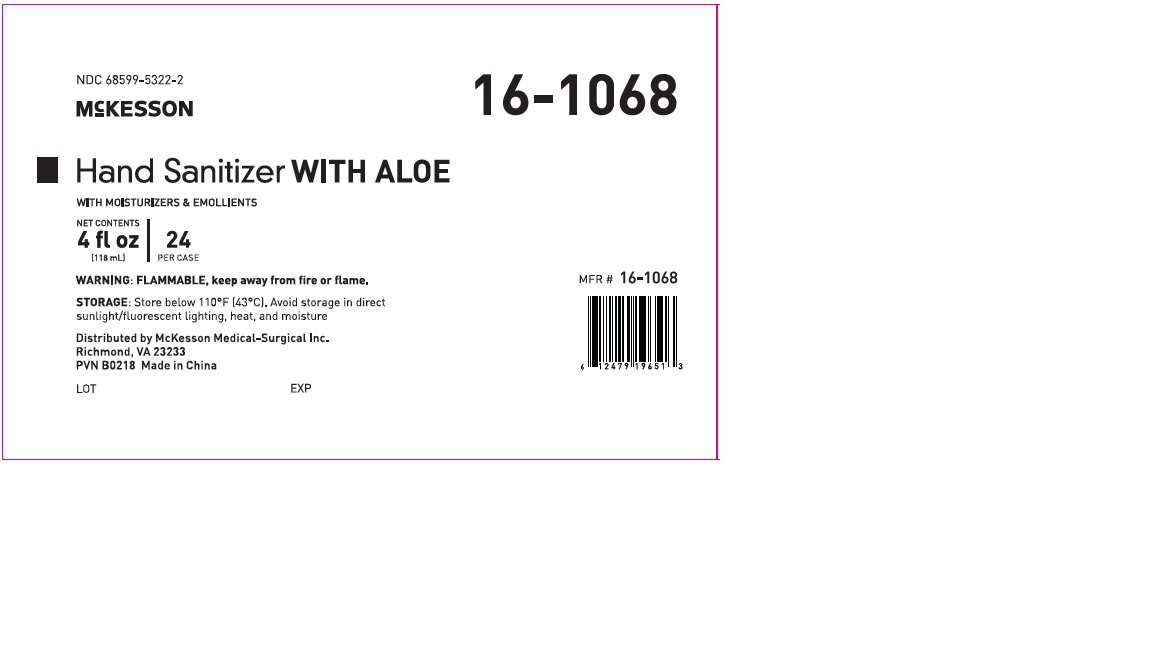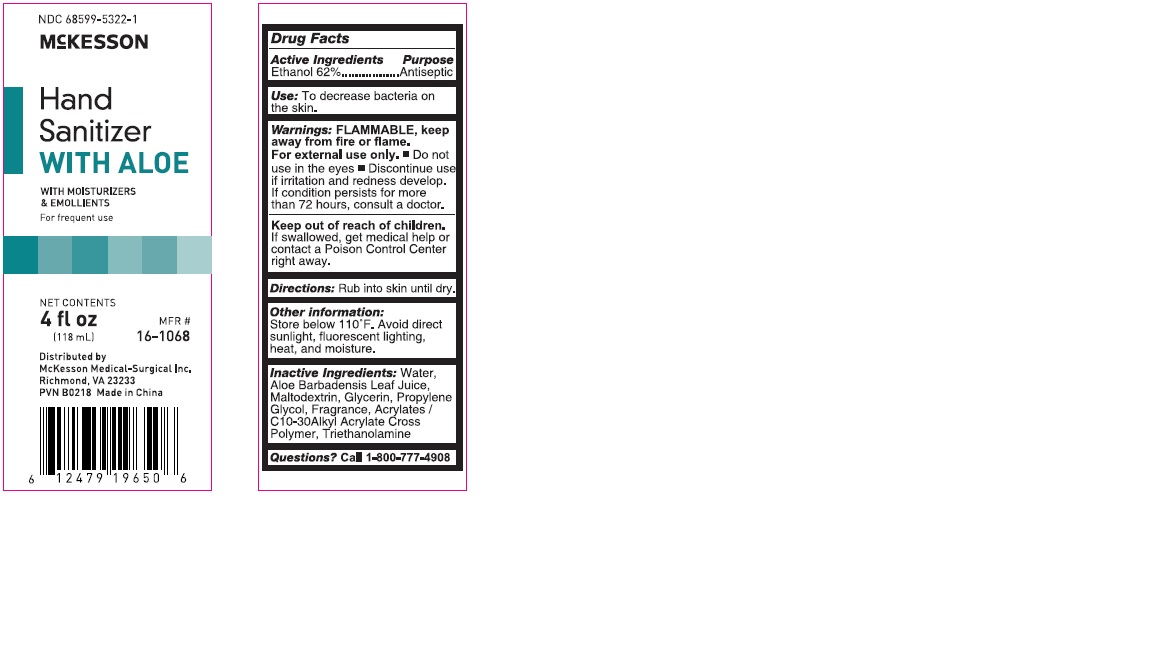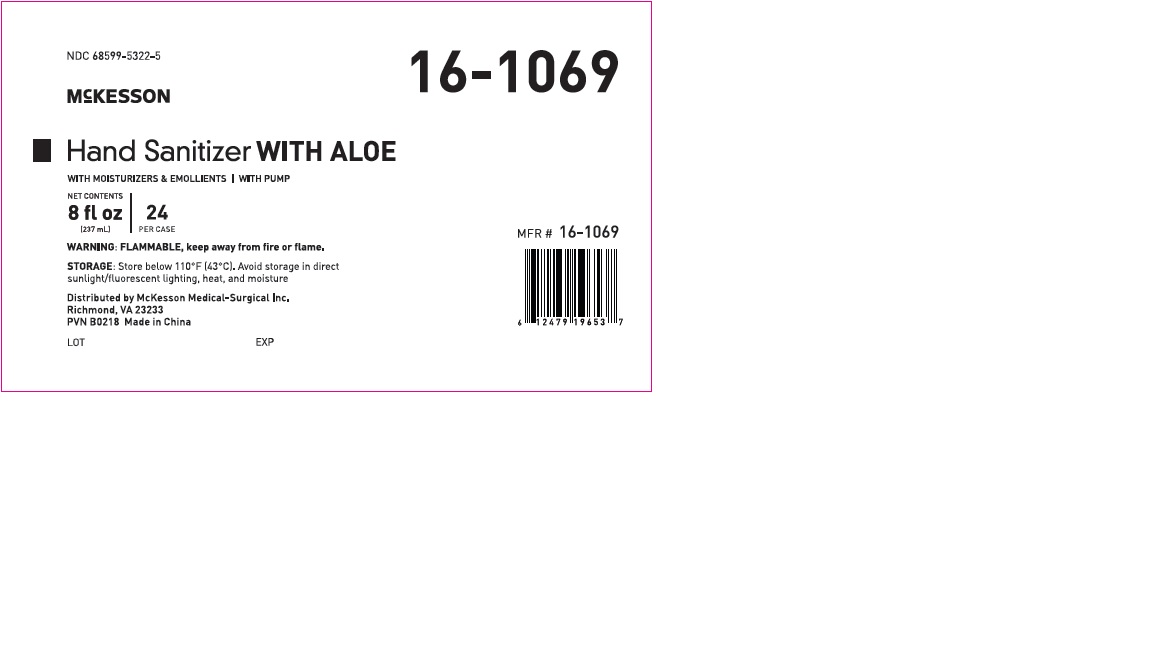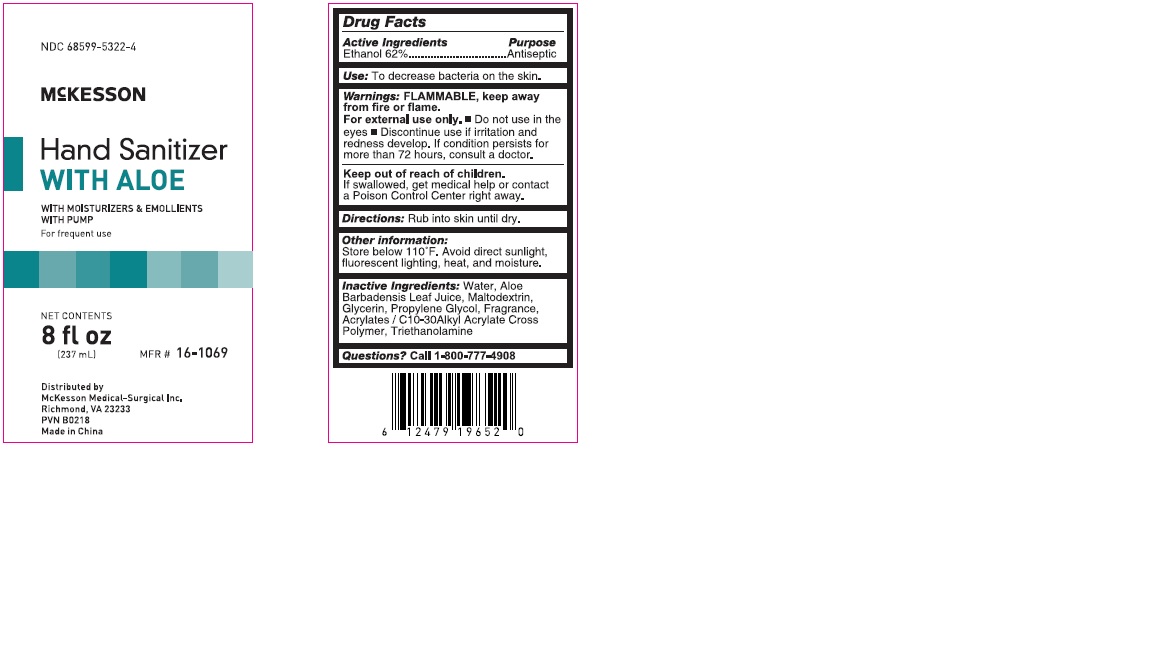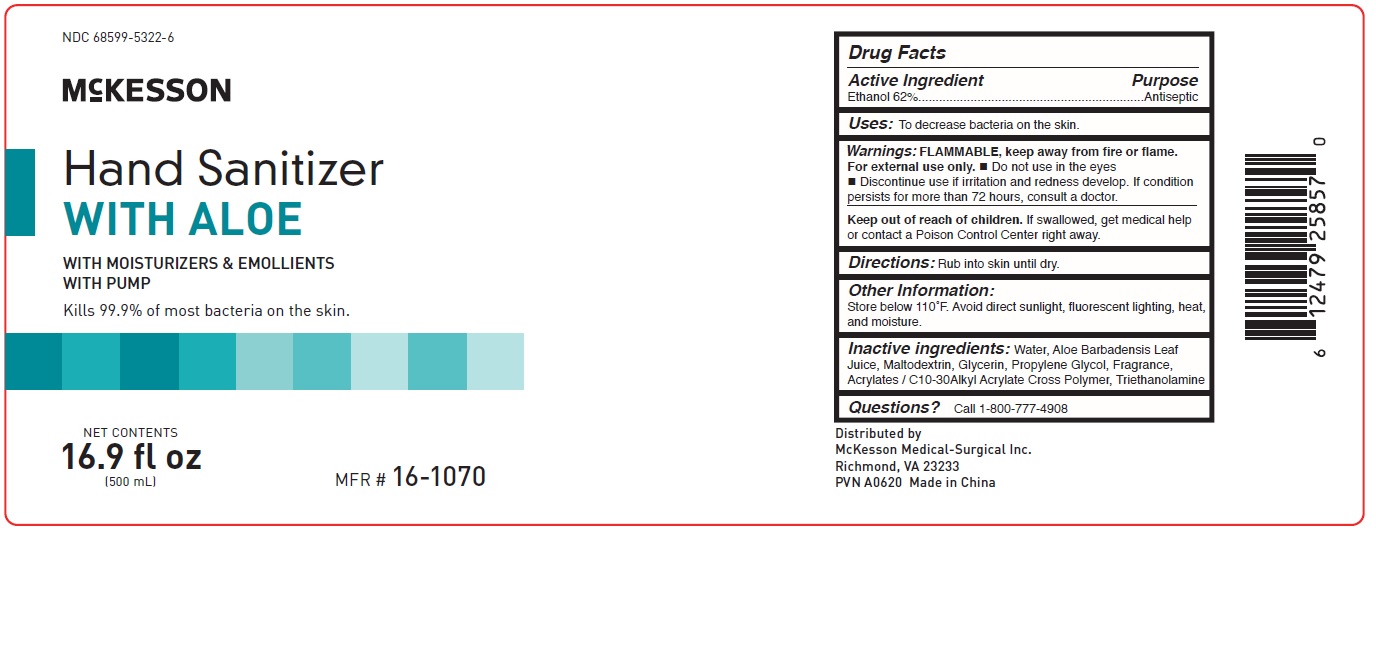 DRUG LABEL: Antiseptic
NDC: 68599-5322 | Form: GEL
Manufacturer: McKesson
Category: otc | Type: HUMAN OTC DRUG LABEL
Date: 20241011

ACTIVE INGREDIENTS: ALCOHOL 0.62 mL/1 mL
INACTIVE INGREDIENTS: ALOE VERA LEAF; CARBOMER INTERPOLYMER TYPE A (55000 CPS); TROLAMINE; WATER; MALTODEXTRIN; GLYCERIN; PROPYLENE GLYCOL

Hand Sanitizer with Aloe

Drug Facts

Active Ingredients

Ethanol 62%

Purpose

Antiseptic

Use:

To decrease bacteria on the skin.

Warnings:

FLAMMABLE, keep away from fire or flame.

For external use only.

- Do not use in the eyes
- Discontinue use if irritation and redness develop. If condition persists for more than 72 hours, consult a doctor.

Keep out of reach of children.

If swallowed, get medical help or contact a Poison Control Center right away.

DOSAGE AND ADMINISTRATION

Directions:Rub into skin until dry.

Other Information:

Store below 110F. Avoid direct sunlight, fluorescent lighting, heat, and moisture.

Inactive Ingredients:

Water, Aloe Barbadensis Leaf Juice, Maltodextrin,
Glycerin, Propylene Glycol, Fragrance,
Acrylates/C10-30 Alkyl Acrylate Cross Polymer,
Triethanolamine

Questions:

Call 1-800-777-4908

PACKAGE LABEL

NDC 68599-5322-1

McKesson Hand Sanitizer

With Aloe

With Moisturizers and Emollients

For frequent use

Net Content

4 fl oz (118mL)

MFR# 16-1068

NDC 68599-5322-2

McKesson Hand Sanitizer

With Aloe

With Moisturizers and Emollients

For frequent use

Net Content

4 fl oz (118mL)

24 per case

Warning: Flammable, keep away from fire or flame

Store below 110F (43C)

PACKAGE LABEL

NDC 68599-5322-4

McKesson Hand Sanitizer

With Aloe

With Moisturizers and Emollients with Pump

For frequent use

Net Content

8 fl oz (237mL)

MFR# 16-1069

NDC 68599-5322-5

McKesson Hand Sanitizer

With Aloe

With Moisturizers and Emollients with Pump

Net Content

8 fl oz (237mL)

24 per Case

MFR# 16-1069

Warning: Flammable, keep away from fire or flame.

PACKAGE LABEL

NDC 68599-5322-6

McKesson

Hand Sanitizers with Aloe

16.9 fl oz (500mL)

12 per case

MFR# 16-1070